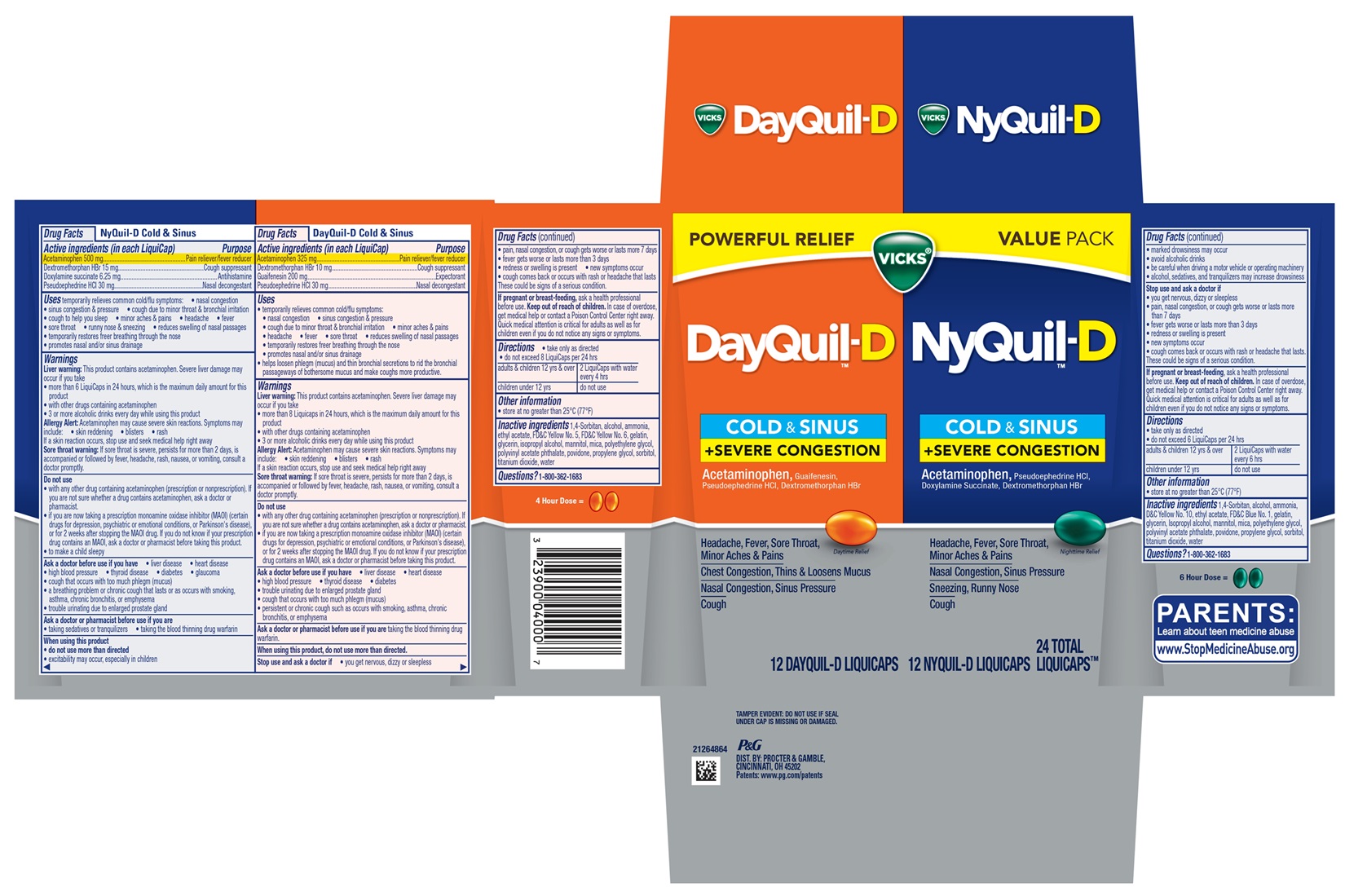 DRUG LABEL: Vicks DayQuil-D NyQuil-D
NDC: 84126-365 | Form: KIT | Route: ORAL
Manufacturer: The Procter & Gamble Manufacturing Company
Category: otc | Type: HUMAN OTC DRUG LABEL
Date: 20250811

ACTIVE INGREDIENTS: GUAIFENESIN 200 mg/1 1; PSEUDOEPHEDRINE HYDROCHLORIDE 30 mg/1 1; DEXTROMETHORPHAN HYDROBROMIDE 10 mg/1 1; ACETAMINOPHEN 325 mg/1 1; ACETAMINOPHEN 500 mg/1 1; DEXTROMETHORPHAN HYDROBROMIDE 15 mg/1 1; DOXYLAMINE SUCCINATE 6.25 mg/1 1; PSEUDOEPHEDRINE HYDROCHLORIDE 30 mg/1 1
INACTIVE INGREDIENTS: 1,4-SORBITAN; POLYVINYL ACETATE PHTHALATE; ALCOHOL; AMMONIA; ETHYL ACETATE; ISOPROPYL ALCOHOL; MANNITOL; PROPYLENE GLYCOL; WATER; SORBITOL; GLYCERIN; POVIDONE; TITANIUM DIOXIDE; MICA; FD&C YELLOW NO. 5; GELATIN; FD&C YELLOW NO. 6; POLYETHYLENE GLYCOL, UNSPECIFIED; MICA; GELATIN; ALCOHOL; AMMONIA; ETHYL ACETATE; MANNITOL; ISOPROPYL ALCOHOL; POLYVINYL ACETATE PHTHALATE; PROPYLENE GLYCOL; POLYETHYLENE GLYCOL, UNSPECIFIED; FD&C BLUE NO. 1; GLYCERIN; WATER; TITANIUM DIOXIDE; POVIDONE; D&C YELLOW NO. 10; SORBITOL; 1,4-SORBITAN

VICKS® DayQuil-D™ NyQuil-D™ LiquiCaps™ COLD & SINUS + SEVERE CONGESTION
Convenience Pack

Vicks®DayQuil-D™ Cold & Sinus + Severe Congestion, Liquicaps

Drug Facts

Active Ingredient (in each LiquiCap)

Acetaminophen 325 mg

Dextromethorphan HBr 10 mg

Guaifenesin 200 mg

Pseudoephedrine HCl 30 mg

Purpose

Pain reliever/fever reducer

Cough suppressant

Expectorant

Nasal decongestant

Uses

temporarily relieves common cold/flu symptoms:

- nasal congestion
- sinus congestion & pressure
- cough due to minor throat & bronchial irritation
- minor aches & pains
- headache
- fever
- sore throat
- reduces swelling of nasal passages
- temporarily restores freer breathing through the nose
- promotes nasal and/or sinus drainage
- helps loosen phlegm (mucus) and thin bronchial secretions to rid the bronchial passageways of bothersome mucus and make coughs more productive.

Warnings

Liver warning: This product contains acetaminophen.

Severe liver damage may occur if you take

- more than 8 Liquicaps in 24 hours, which is the maximum daily amount for this product
- with other drugs containing acetaminophen
- 3 or more alcoholic drinks every day while using this product

Allergy Alert: Acetaminophen may cause severe skin reactions.

Symptoms may include:

- skin reddening
- blisters
- rash

If a skin reaction occurs, stop use and seek medical help right away

Sore throat warning: If sore throat is severe, persists for more than 2 days, is accompanied or followed by fever, headache, rash, nausea, or vomiting, consult a doctor promptly.

Do not use

- with any other drug containing acetaminophen (prescription or nonprescription). If you are not sure whether a drug contains acetaminophen, ask a doctor or pharmacist.
- if you are now taking a prescription monoamine oxidase inhibitor (MAOI) (certain drugs for depression, psychiatric or emotional conditions, or Parkinson's disease), or for 2 weeks after stopping the MAOI drug. If you do not know if your prescription drug contains an MAOI, ask a doctor or pharmacist before taking this product.

Ask a doctor before use if you have

- liver disease
- heart disease
- high blood pressure
- thyroid disease
- diabetes
- trouble urinating due to enlarged prostate gland
- cough that occurs with too much phlegm (mucus)
- persistent or chronic cough such as occurs with smoking, asthma, or emphysema

Ask a doctor or pharmacist before use if you are

taking the blood thinning drug warfarin

Stop use and ask a doctor if

- you get nervous, dizzy or sleepless
- pain, nasal congestion, or cough gets worse or lasts more than 7 days
- fever gets worse or lasts more than 3 days
- redness or swelling is present
- new symptoms occur
- cough comes back or occurs with rash or headache that lasts.

These could be signs of a serious condition.

If pregnant or breast-feeding,

ask a health professional before use.

OVERDOSAGE

In case of overdose, get medical help or contact a Poison Control Center right away. Quick medical attention is critical for adults as well as for children even if you do not notice any signs or symptoms.

Directions

• take only as directed

• do not exceed 8 LiquiCaps per 24 hrs

adults & children 12 yrs & over | 2 LiquiCaps with water every 4 hrs
children under 12 yrs | do not use

Other information

- store at no greater than 25°C (77°F)

Inactive ingredients

1,4-Sorbitan, alcohol, ammonia, ethyl acetate, FD&C Yellow No. 5, FD&C Yellow No. 6, gelatin, glycerin, isopropyl alcohol, mannitol, mica, polyethylene glycol, polyvinyl acetate phthalate, povidone, propylene glycol, sorbitol, titanium dioxide, water

Questions?

1-800-362-1683

TAMPER EVIDENT: DO NOT USE IF SEAL UNDER CAP IS MISSING OR DAMAGED.

DIST. BY PROCTER & GAMBLE,

CINCINNATI OH 45202

Vicks®NyQuil-D™ Cold & Sinus + Severe Congestion, Liquicaps

Drug Facts

Active Ingredient (in each LiquiCap)

Acetaminophen 500 mg

Dextromethorphan HBr 15 mg

Doxylamine succinate 6.25 mg

Pseudoephedrine HCl 30 mg

Purpose

Pain reliever/fever reducer

Cough suppressant

Antihistamine

Nasal decongestant

Uses

temporarily relieves common cold/flu symptoms:

- nasal congestion
- sinus congestion & pressure
- cough due to minor throat & bronchial irritation
- cough to help you sleep • minor aches & pains
- headache
- fever
- sore throat
- runny nose & sneezing
- reduces swelling of nasal passages
- temporarily
- restores freer breathing through the nose
- promotes nasal and/or sinus drainage

Warnings

Liver warning: This product contains acetaminophen.

Severe liver damage may occur if you take

- more than 8 Liquicaps in 24 hours, which is the maximum daily amount for this product
- with other drugs containing acetaminophen
- 3 or more alcoholic drinks every day while using this product

Allergy Alert: Acetaminophen may cause severe skin reactions.

Symptoms may include:

- skin reddening
- blisters
- rash

If a skin reaction occurs, stop use and seek medical help right away

Sore throat warning: If sore throat is severe, persists for more than 2 days, is accompanied or followed by fever, headache, rash, nausea, or vomiting, consult a doctor promptly.

Do not use

- with any other drug containing acetaminophen (prescription or nonprescription). If you are not sure whether a drug contains acetaminophen, ask a doctor or pharmacist.
- if you are now taking a prescription monoamine oxidase inhibitor (MAOI) (certain drugs for depression, psychiatric or emotional conditions, or Parkinson's disease), or for 2 weeks after stopping the MAOI drug. If you do not know if your prescription drug contains an MAOI, ask a doctor or pharmacist before taking this product.

Ask a doctor before use if you have

- liver disease
- heart disease
- high blood pressure
- thyroid disease
- diabetes
- glaucoma
- cough that occurs with too much phlegm (mucus)
- a breathing problem or chronic cough that lasts or as occurs with smoking, asthma, chronic bronchitis, or emphysema
- trouble urinating due to enlarged prostate gland

Ask a doctor or pharmacist before use if you are

- taking sedatives or tranquilizers
- taking the blood thinning drug warfarin

When using this product

- do not use more than directed
- excitability may occur, especially in children
- marked drowsiness may occur
- avoid alcoholic drinks
- be careful when driving a motor vehicle or operating machinery
- alcohol, sedatives, and tranquilizers may increase drowsiness

Stop use and ask a doctor if

- you get nervous, dizzy or sleepless
- pain, nasal congestion, or cough gets worse or lasts more than 7 days
- fever gets worse or lasts more than 3 days
- redness or swelling is present
- new symptoms occur
- cough comes back or occurs with rash or headache that lasts.

These could be signs of a serious condition.

If pregnant or breast-feeding,

ask a health professional before use.

In case of overdose, get medical help or contact a Poison Control Center right away. Quick medical attention is critical for adults as well as for children even if you do not notice any signs or symptoms.

Directions

- take only as directed
- do not exceed 6 LiquiCaps per 24 hrs

adults & children 12 yrs & over | 2 LiquiCaps with water every 6 hrs
children under 12 yrs | do not use

Other information

store at no greater than 25°C (77°F)

Inactive ingredients

1,4-Sorbitan, alcohol, ammonia, D&C Yellow No. 10, ethyl acetate, FD&C Blue No. 1, gelatin, glycerin, Isopropyl alcohol, mannitol, mica, polyethylene glycol, polyvinyl acetate phthalate, povidone, propylene glycol, sorbitol, titanium dioxide, water

Questions?

1-800-362-1683

TAMPER EVIDENT: DO NOT USE IF SEAL UNDER CAP IS MISSING OR DAMAGED.

DIST. BY PROCTER & GAMBLE,

CINCINNATI OH 45202

PRINCIPAL DISPLAY PANEL

POWERFUL RELIEF

VALUE PACK

VICKS®

DayQuil-D

COLD & SINUS

+ SEVERE CONGESTION

Acetaminophen, Guaifenesin, Pseudoephedrine HCl, Dextromethorphan HBr

Headache, Fever, Sore Throat, Minor Aches & Pains

Chest Congestion, Thins & Loosens Mucus

Nasal Congestion, Sinus Pressure

Cough

Daytime Relief

12 LIQUICAPS™

VICKS®

NyQuil-D

COLD & SINUS

+ SEVERE CONGESTION

Acetaminophen, Pseudoephedrine HCl, Doxylamine Succinate, Dextromethorphan HBr

Headache, Fever, Sore Throat, Minor Aches & Pains

Nasal Congestion, Sinus Pressure

Sneezing, Runny Nose

Cough

Nighttime Relief

12 LIQUICAPS™

12 DAYQUIL-D LIQUICAPS™ 12 NYQUIL-D LIQUICAPS™ 24 TOTAL LIQUICAPS™